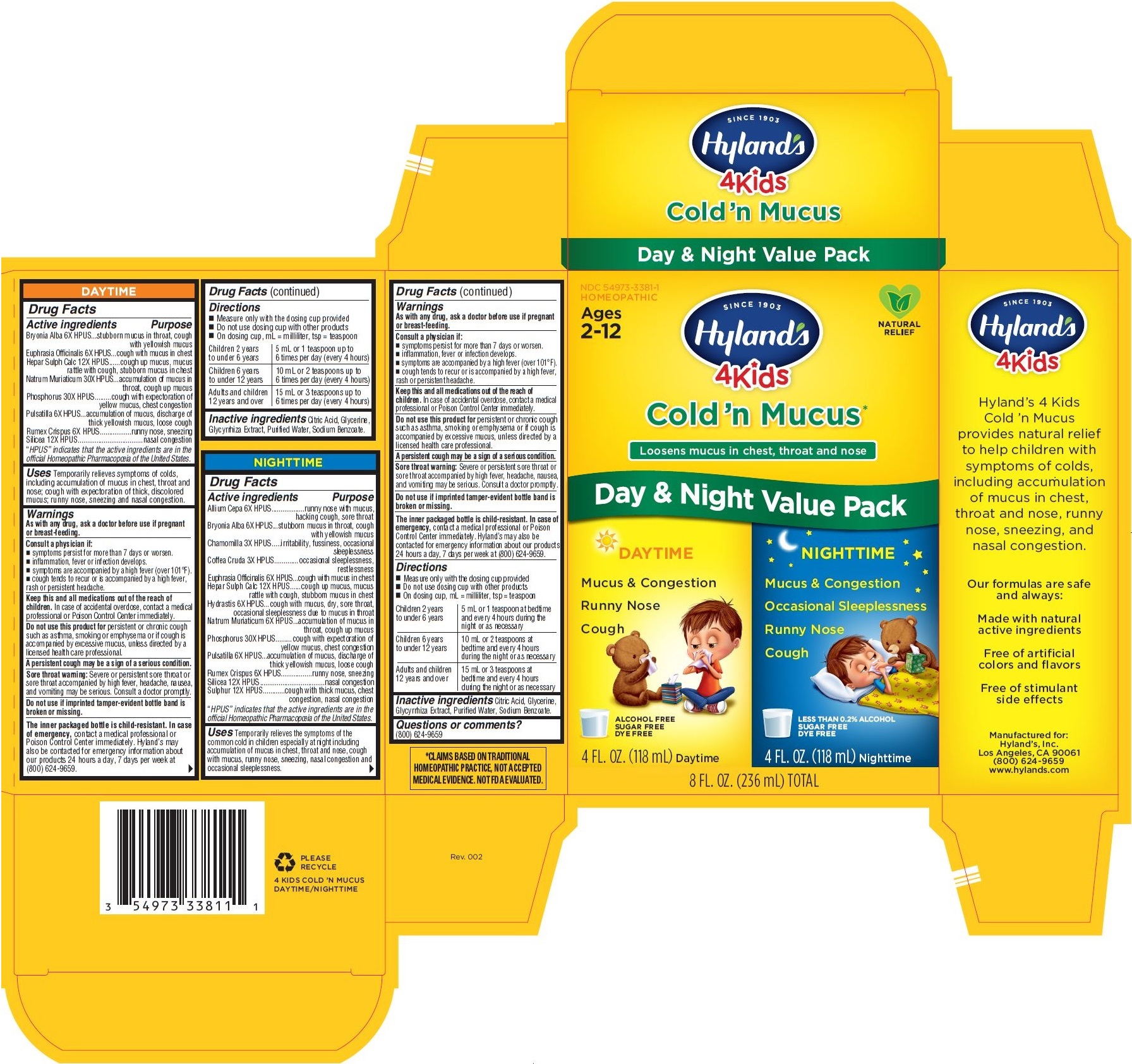 DRUG LABEL: 4 Kids Cold and Mucus
NDC: 54973-3381 | Form: KIT | Route: ORAL
Manufacturer: Hyland's Inc.
Category: homeopathic | Type: HUMAN OTC DRUG LABEL
Date: 20221122

ACTIVE INGREDIENTS: MATRICARIA CHAMOMILLA 3 [hp_X]/1 mL; SODIUM CHLORIDE 6 [hp_X]/1 mL; SULFUR 12 [hp_X]/1 mL; RUMEX CRISPUS ROOT 6 [hp_X]/1 mL; ONION 6 [hp_X]/1 mL; BRYONIA ALBA ROOT 6 [hp_X]/1 mL; EUPHRASIA STRICTA 6 [hp_X]/1 mL; GOLDENSEAL 6 [hp_X]/1 mL; PHOSPHORUS 30 [hp_X]/1 mL; ARABICA COFFEE BEAN 3 [hp_X]/1 mL; CALCIUM SULFIDE 12 [hp_X]/1 mL; SILICON DIOXIDE 12 [hp_X]/1 mL; ANEMONE PULSATILLA 6 [hp_X]/1 mL; EUPHRASIA STRICTA 6 [hp_X]/1 mL; BRYONIA ALBA ROOT 6 [hp_X]/1 mL; ANEMONE PULSATILLA 6 [hp_X]/1 mL; SODIUM CHLORIDE 30 [hp_X]/1 mL; PHOSPHORUS 30 [hp_X]/1 mL; SILICON DIOXIDE 12 [hp_X]/1 mL; RUMEX CRISPUS ROOT 6 [hp_X]/1 mL; CALCIUM SULFIDE 12 [hp_X]/1 mL
INACTIVE INGREDIENTS: GLYCYRRHIZA GLABRA; SODIUM BENZOATE; WATER; CITRIC ACID MONOHYDRATE; GLYCERIN; SODIUM BENZOATE; GLYCERIN; WATER; CITRIC ACID MONOHYDRATE; GLYCYRRHIZA GLABRA

4 Kids Cold'n Mucus Value Pack

DAYTIME

Drug Facts

Active ingredients

Bryonia Alba 6X HPUS

Euphrasia Officinalis 6X HPUS

Hepar Sulph Calc 12X HPUS

Natrum Muriaticum 30X HPUS

Phosphorus 30X HPUS

Pulsatilla 6X HPUS

Rumex Crispus 6X HPUS

Silicea 12X HPUS

“HPUS” indicates that the active ingredients are in the official Homeopathic Pharmacopoeia of the United States.

PURPOSE

Bryonia Alba 6X HPUS...stubborn mucus in throat, cough with yellowish mucus

Euphrasia Officinalis 6X HPUS...cough with mucus in chest

Hepar Sulph Calc 12X HPUS......cough up mucus, mucus rattle with cough, stubborn mucus in chest

Natrum Muriaticum 30X HPUS.....accumulation of mucus in throat, cough up mucus

Phosphorus 30X HPUS.........cough with expectoration of yellow mucus, chest congestion

Pulsatilla 6X HPUS...accumulation of mucus, discharge of thick yellowish mucus, loose cough

Rumex Crispus 6X HPUS.................runny nose, sneezing

Silicea 12X HPUS...................................nasal congestion

Uses

Temporarily relieves symptoms of colds, including accumulation of mucus in chest, throat and nose; cough with expectoration of thick, discolored mucus; runny nose, sneezing and nasal congestion.

Warnings

PREGNANCY OR BREAST FEEDING

As with any drug, ask a doctor before use if pregnant or breast-feeding.

ASK DOCTOR

Consult a physician if:

- symptoms persist for more than 7 days or worsen.
- inflammation, fever or infection develops.
- symptoms are accompanied by a high fever (over 101°F).
- cough tends to recur or is accompanied by a high fever,rash or persistent headache.

KEEP OUT OF REACH OF CHILDREN

Keep this and all medications out of the reach of children. In case of accidental overdose, contact a medical professional or Poison Control Center immediately.

Do not use this product for persistent or chronic cough such as asthma, smoking or emphysema or if cough is accompanied by excessive mucus, unless directed by a licensed health care professional.

A persistent cough may be a sign of a serious condition.

Sore throat warning

Severe or persistent sore throat or sore throat accompanied by high fever, headache, nausea, and vomiting may be serious. Consult a doctor promptly.

Do not use if imprinted tamper-evident bottle band is broken or missing.

The inner packaged bottle is child-resistant. In case of emergency, contact a medical professional or Poison Control Center immediately. Hyland’s may also be contacted for emergency information about our products 24 hours a day, 7 days per week at (800) 624-9659.

Drug Facts (continued)

Directions

- Measure only with the dosing cup provided
- Do not use dosing cup with other products
- On dosing cup, mL = milliliter, tsp = teaspoon

Children 2 years; to under 6 years | 5 mL or 1 teaspoon up to; 6 times per day (every 4 hours)
Children 6 years; to under 12 years | 10 mL or 2 teaspoons up to; 6 times per day (every 4 hours)
Adults and children; 12 years and over | 15 mL or 3 teaspoons up to; 6 times per day (every 4 hours)

Inactive ingredients

Citric Acid, Glycerine, Glycyrrhiza Extract, Purified Water, Sodium Benzoate.

NIGHTTIME

Active ingredients

Allium Cepa 6X HPUS

Bryonia Alba 6X HPUS

Chamomilla 3X HPUS

Coffea Cruda 3X HPUS

Euphrasia Officinalis 6X HPUS

Hepar Sulph Calc 12X HPUS

Hydrastis 6X HPUS

Natrum Muriaticum 6X HPUS

Phosphorus 30X HPUS

Pulsatilla 6X HPUS

Rumex Crispus 6X HPUS

Silicea 12X HPUS

Sulphur 12X HPUS

“HPUS” indicates that the active ingredients are in the official Homeopathic Pharmacopœia of the United States.

PURPOSE

Allium Cepa 6X HPUS..................runny nose with mucus, hacking cough, sore throat

Bryonia Alba 6X HPUS...stubborn mucus in throat, cough with yellowish mucus

Chamomilla 3X HPUS.....irritability, fussiness, occasional sleeplessness

Coffea Cruda 3X HPUS.............occasional sleeplessness, restlessness

Euphrasia Officinalis 6X HPUS...cough with mucus in chest

Hepar Sulph Calc 12X HPUS......cough up mucus, mucus rattle with cough, stubborn mucus in chest

Hydrastis 6X HPUS...cough with mucus, dry, sore throat, occasional sleeplessness due to mucus in throat

Natrum Muriaticum 6X HPUS...accumulation of mucus in throat, cough up mucus

Phosphorus 30X HPUS.........cough with expectoration of yellow mucus, chest congestion

Pulsatilla 6X HPUS...accumulation of mucus, discharge of thick yellowish mucus, loose cough

Rumex Crispus 6X HPUS.................runny nose, sneezing

Silicea 12X HPUS...................................nasal congestion

Sulphur 12X HPUS............cough with thick mucus, chest congestion, nasal congestion

Uses

Temporarily relieves the symptoms of the common cold in children especially at night including accumulation of mucus in chest, throat and nose, cough with mucus, runny nose, sneezing, nasal congestion and occasional sleeplessness.

Drug Facts (continued)

Warnings

PREGNANCY OR BREAST FEEDING

As with any drug, ask a doctor before use if pregnant or breast-feeding.

ASK DOCTOR

Consult a physician if:

- symptoms persist for more than 7 days or worsen.
- inflammation, fever or infection develops.
- symptoms are accompanied by a high fever (over 101°F).
- cough tends to recur or is accompanied by a high fever,rash or persistent headache.

KEEP OUT OF REACH OF CHILDREN

Keep this and all medications out of the reach of children. In case of accidental overdose, contact a medical professional or Poison Control Center immediately.

Do not use this product for persistent or chronic cough such as asthma, smoking or emphysema or if cough is accompanied by excessive mucus, unless directed by a licensed health care professional.

A persistent cough may be a sign of a serious condition.

Sore throat warning

Severe or persistent sore throat or sore throat accompanied by high fever, headache, nausea, and vomiting may be serious. Consult a doctor promptly.

Do not use if imprinted tamper-evident bottle band is broken or missing.

The inner packaged bottle is child-resistant. In case of emergency, contact a medical professional or Poison

Control Center immediately. Hyland’s may also be contacted for emergency information about our products

24 hours a day, 7 days per week at (800) 624-9659.

Directions

- Measure only with the dosing cup provided
- Do not use dosing cup with other products
- On dosing cup, mL = milliliter, tsp = teaspoon

Children 2 years; to under 6 years | 5 mL or 1 teaspoon at bedtime; and every 4 hours during the; night or as necessary
Children 6 years; to under 12 years | 10 mL or 2 teaspoons at; bedtime and every 4 hours; during the night or as necessary
Adults and children; 12 years and over | 15 mL or 3 teaspoons at; bedtime and every 4 hours; during the night or as necessary

Inactive ingredients

Citric Acid, Glycerine, Glycyrrhiza Extract, Purified Water, Sodium Benzoate.

Questions or comments?

(800) 624-9659

*CLAIMS BASED ON TRADITIONAL

HOMEOPATHIC PRACTICE, NOT ACCEPTED

MEDICAL EVIDENCE. NOT FDA EVALUATED.

Principal Display Panel - Kit Carton

NDC 54973-3381-1

HOMEOPATHIC

Ages

2-12

NATURAL

RELIEF

SINCE 1903

Hyland's

4 Kids

Cold'n Mucus*

Loosens mucus in chest, throat and nose

Day & Night Value Pack

DAYTIME

Mucus & Congestion

Runny Nose

Cough

ALCOHOL FREE

SUGAR FREE

DYE FREE

4 FL. OZ. (118 mL) Daytime

NIGHTTIME

Mucus & Congestion

Occasional Sleeplessness

Runny Nose

Cough

LESS THAN 0.2% ALCOHOL

SUGAR FREE

DYE FREE

4 FL. OZ. (118 mL) Nighttime

8 FL. OZ. (236 mL) TOTAL